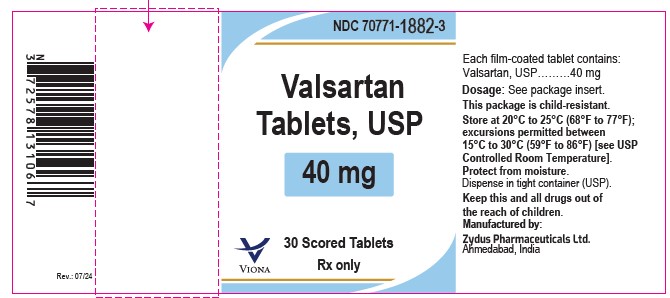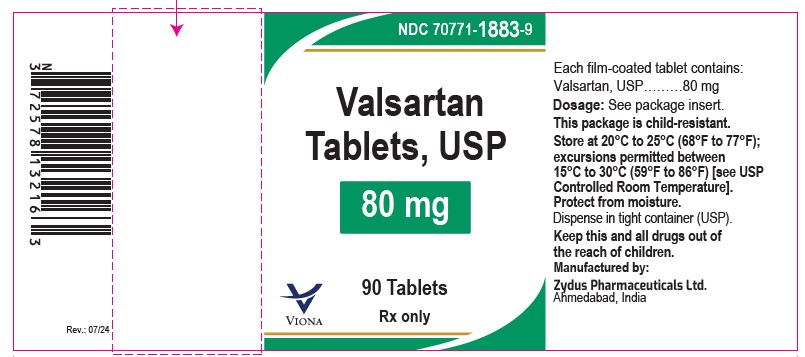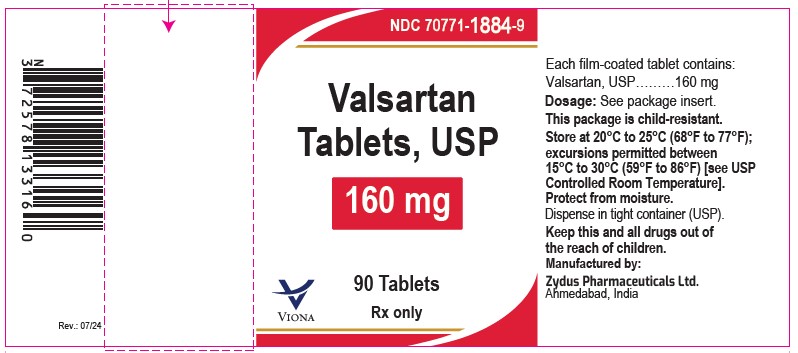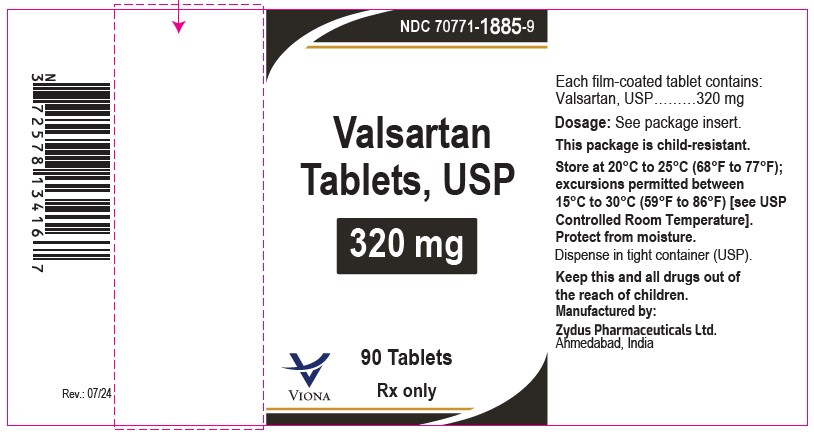 DRUG LABEL: Valsartan
NDC: 70771-1882 | Form: TABLET, FILM COATED
Manufacturer: Zydus Lifesciences Limited
Category: prescription | Type: HUMAN PRESCRIPTION DRUG LABEL
Date: 20240723

ACTIVE INGREDIENTS: VALSARTAN 40 mg/1 1
INACTIVE INGREDIENTS: CROSPOVIDONE; FERRIC OXIDE YELLOW; HYPROMELLOSE 2910 (6 MPA.S); MAGNESIUM STEARATE; MICROCRYSTALLINE CELLULOSE; POLYETHYLENE GLYCOL 6000; SILICON DIOXIDE; TALC; TITANIUM DIOXIDE

VALSARTAN tablets, for oral use

PACKAGE LABEL.PRINCIPAL DISPLAY PANEL

Valsartan tablets USP, 40 mg

NDC 70771-1882-3

Bottle of 30 Scored Tablets

Rx only

Valsartan tablets USP, 80 mg

NDC 70771-1883-9

Bottle of 90 tablets

Rx only

Valsartan tablets USP, 160 mg

NDC 70771-1884-9

Bottle of 90 tablets

Rx only

Valsartan tablets USP, 320 mg

NDC 70771-1885-9

Bottle of 90 tablets

Rx only